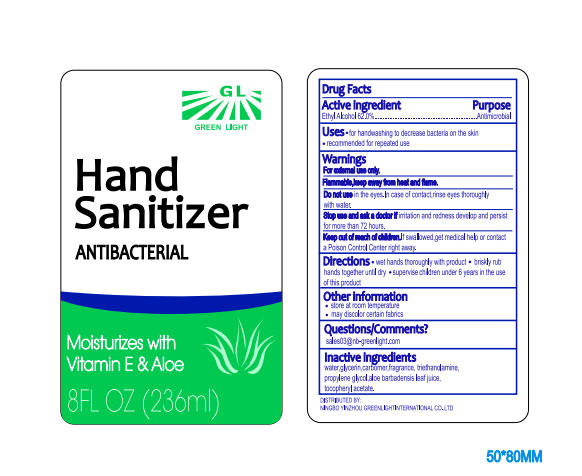 DRUG LABEL: Hand Sanitizer Antibacterial
NDC: 77125-002 | Form: GEL
Manufacturer: Ningbo Yinzhou Lvguang International Trade Co.,Ltd
Category: otc | Type: HUMAN OTC DRUG LABEL
Date: 20200506

ACTIVE INGREDIENTS: ALCOHOL 146.32 mL/236 mL
INACTIVE INGREDIENTS: ALOE VERA LEAF 2.36 mL/236 mL; FD&C YELLOW NO. 5 0.236 mL/236 mL; TRIETHANOLAMINE DODECYLBENZENESULFONATE 2.36 mL/236 mL; TOCOPHEROL 1.18 mL/236 mL; CARBOMER HOMOPOLYMER, UNSPECIFIED TYPE 0.708 mL/236 mL; GLYCERIN 2.36 mL/236 mL; PROPYLENE GLYCOL 2.36 mL/236 mL; WATER 77.88 mL/236 mL; FD&C BLUE NO. 1 0.236 mL/236 mL

Hand Sanitizer Antibacterial

Active Ingredient

Ethyl Alcohol 62.0% Antimicrobial

Purpose

Purpose - Antimicrobial

Uses

- for handwashing to decrease bacteria on the skin
- recommended for repeated use

Warnings

For external use only

Flammable, keep away from heat and flame.

Do not use in the eyes, in case of contact, rinse eyes throughly with water.

Stop use and ask a doctor if irritation and redness develop and persist for more then 72 hours

Keep out of reach children

Keep out of reach of children, If swallowed, get medical help or contact a Poison Control Center right away.

Directions

- wet hands thoughly with product
- briskly rub hands together until dry
- supervise children 6 years of age in the use of this product

Other Information

- store at room temperature
- may discolor certain fabrics

Questions/Comments

sales03@nb-greenlight.com

DISTRIBUTED BY:
NINGBO YINZHOU GREENLIGHT INTERNATIONAL CO.,LTD

Inactive Ingredients

water,glycerin,carbomer, fragrance, triethanolamine, propylene glycol, aloe barbadensis leaf juice, tocopheryl acetate, fd&blue no.1, fd&yellow no.5

Package Label

77125-002-01 NDC 236 ml